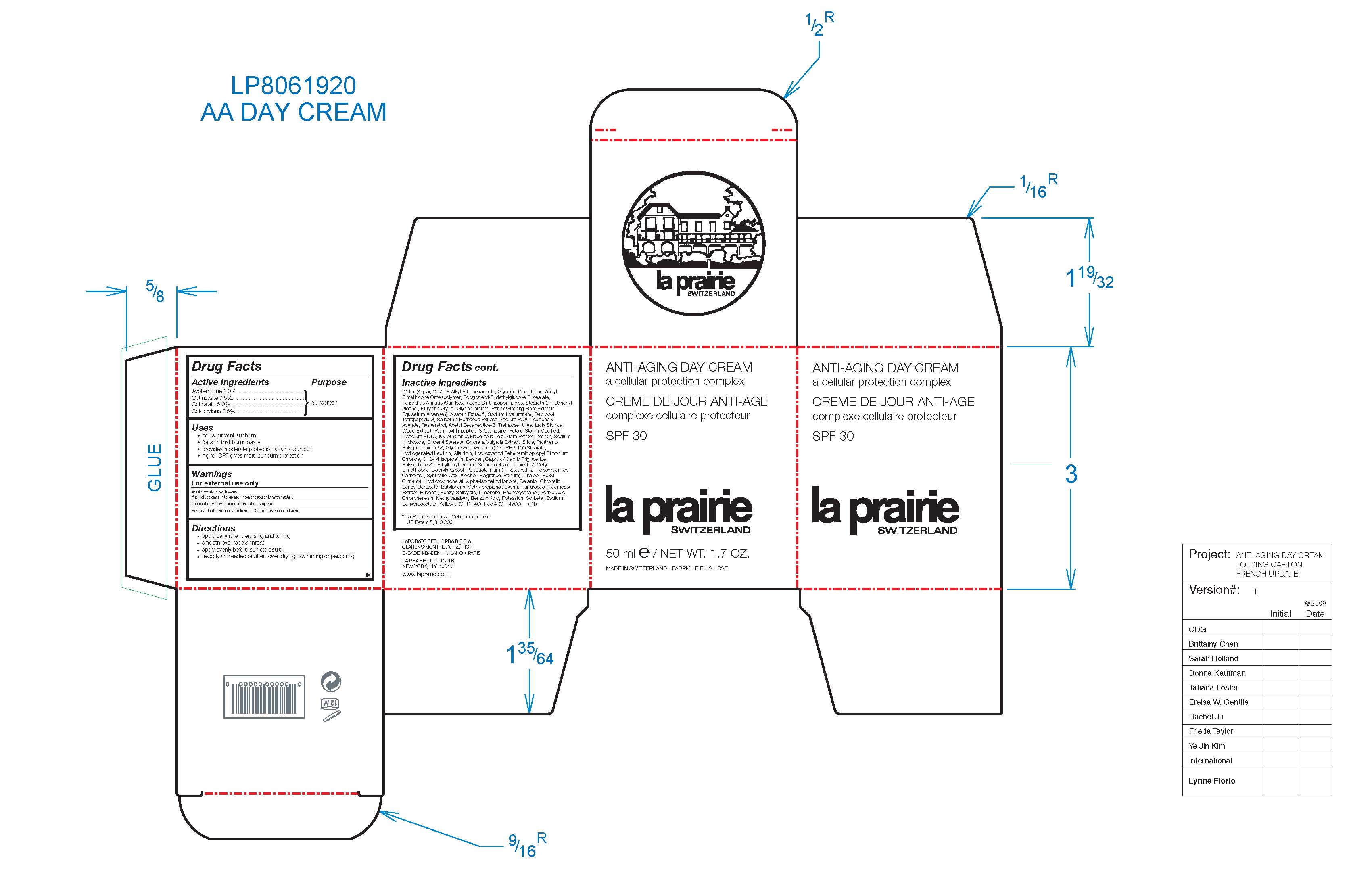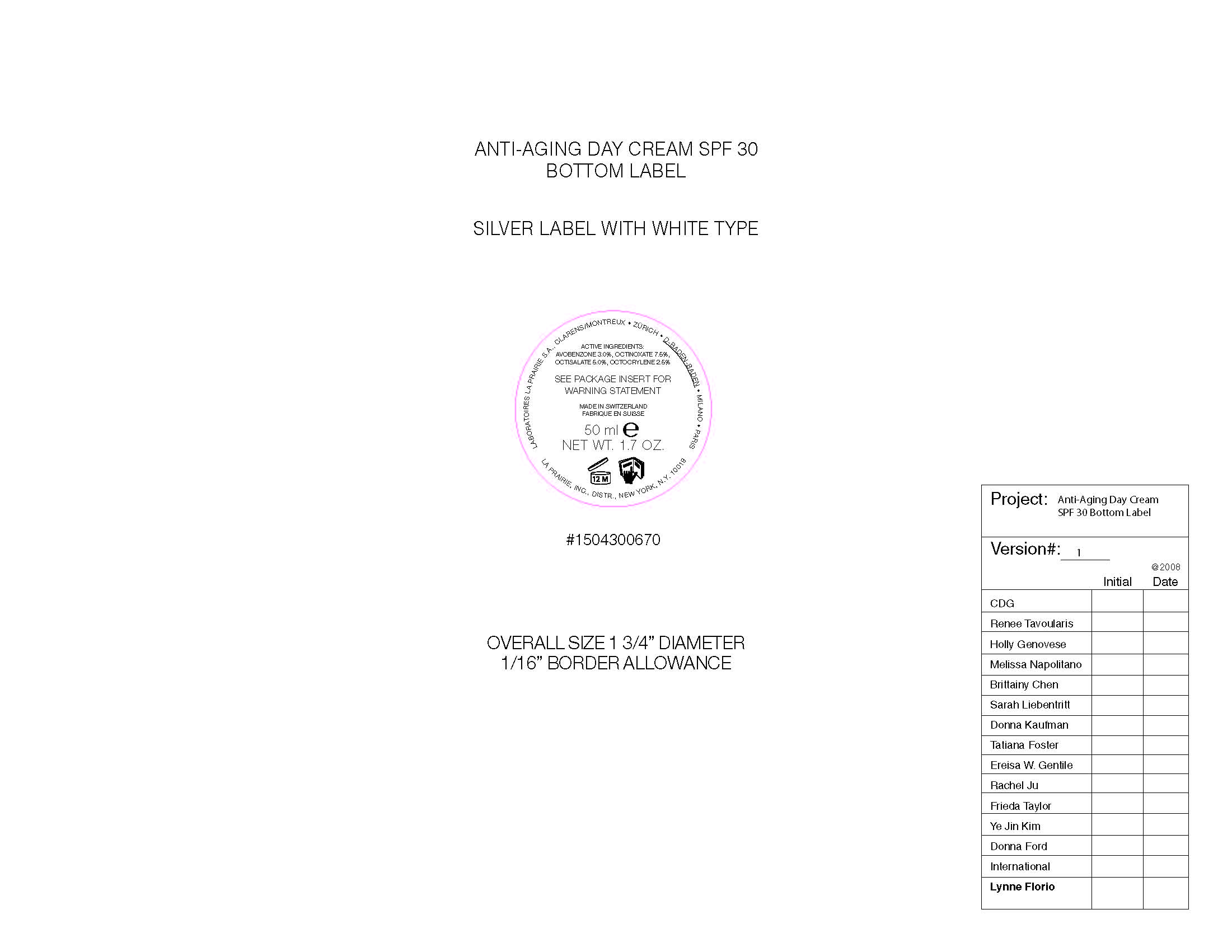 DRUG LABEL: La Prairie Switzerland
NDC: 59614-347 | Form: CREAM
Manufacturer: Juvena Produits de Beaute GMBH
Category: prescription | Type: HUMAN PRESCRIPTION DRUG LABEL
Date: 20100305

ACTIVE INGREDIENTS: AVOBENZONE 3 mL/100 mL; OCTINOXATE 7.5 mL/100 mL; OCTISALATE 5 mL/5 mL; OCTOCRYLENE 2.5 mL/100 mL

Package.Label Principle Display Panel

PACKAGE LABEL

La Prairie Switzerland

Anti-Aging Day Cream

a cellular protection complex

SPF 30

50 ml / NET WT. 1.7 OZ.

Active Ingredients Purpose
Avobenzone 3.0% Sunscreen
Octinoxate 7.5% Sunscreen
Octisalate 5.0% Sunscreen
Octocrylene 2.5% Sunscreen